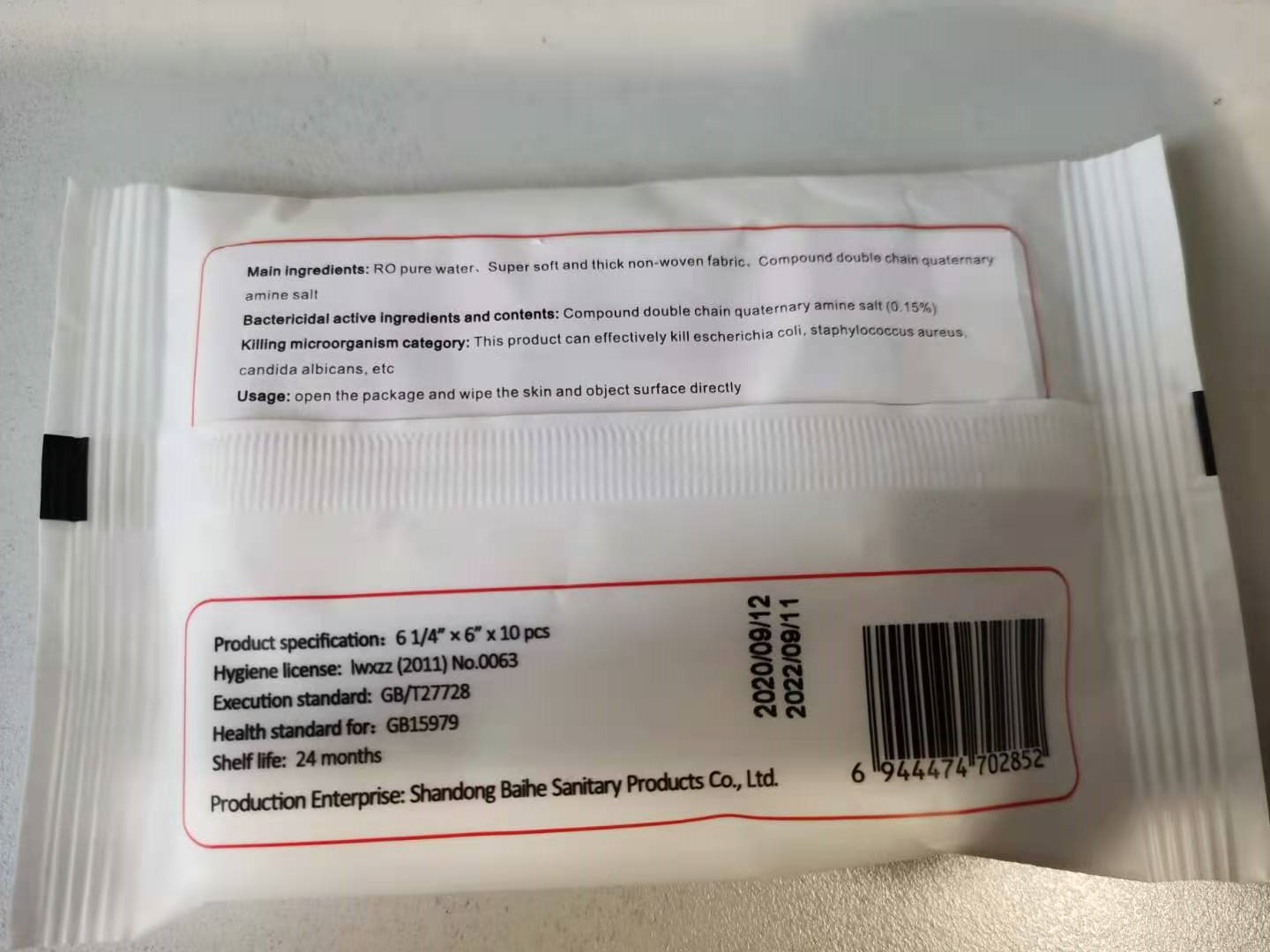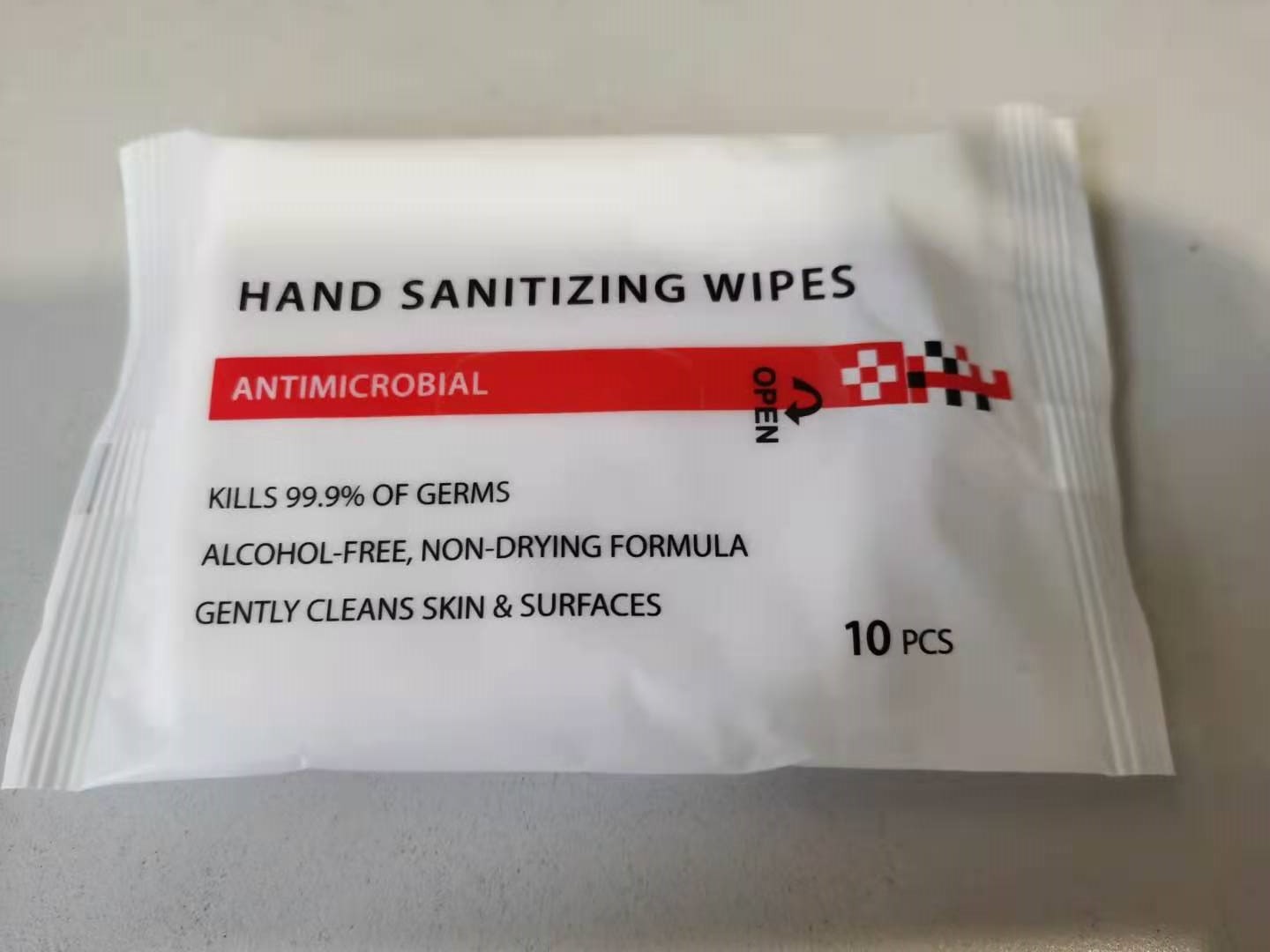 DRUG LABEL: Hand Sanitizing Wipes
NDC: 75428-700 | Form: CLOTH
Manufacturer: Shandong BaiHe Sanitary Products Co., Ltd.
Category: otc | Type: HUMAN OTC DRUG LABEL
Date: 20201123

ACTIVE INGREDIENTS: DIDECYLDIMONIUM CHLORIDE 0.15 1/100 1
INACTIVE INGREDIENTS: WATER

Hand Sanitizing Wipes

Bactericidal active Ingredients and Contents

Compound double chain quaternary amine salt (0.15%)

Purpose

Antibacterial Wipes

Killing microorganism category

This product can effectively kill escherichia coli, staphylococcus aureus, candida albicans, etc.

Warnings

For external use only. Keep away from heat or flame.

Do not use

- in children less than 2 months of age
- on open skin wounds

WHEN USING

In case of contact with eyes, rinse eyes thoroughly. Keep out with water if irritation or rash occurs. If swallowed, get medical help or contact a Poison Control Center right away

Stop use and ask a doctor if irritation or rash occurs.

Keep out of reach of children. If swallowed, get medical help or contact a Poison Control Center right away.

Usage

- Open the package and wipe the skin and object surface directly

Other information

- Dispose of wipe in trash after each use. Avoid freezing and excessive heat above 40°C(104F).

Inactive ingredients

RO pure water, super soft and thick non-woven fabric